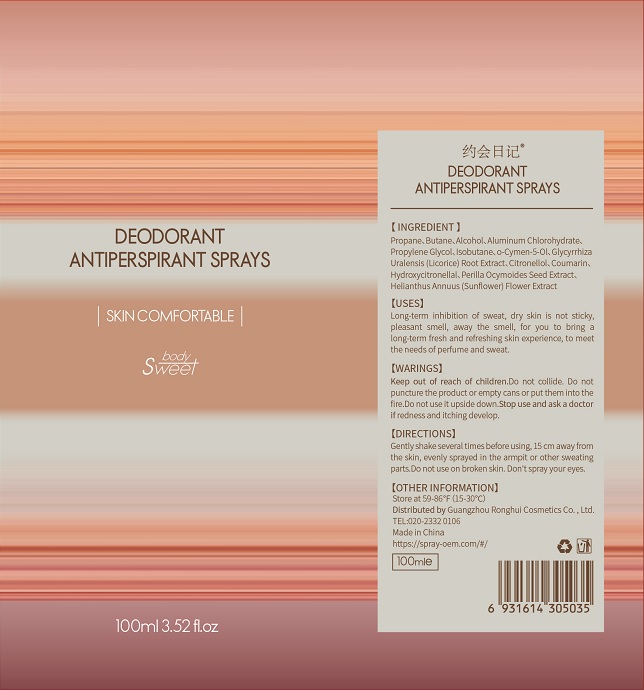 DRUG LABEL: DEODORANT ANTIPERSPIRANT SPRAYS
NDC: 81531-101 | Form: SPRAY
Manufacturer: Guangzhou Ronghui Cosmetics Co., Ltd.
Category: otc | Type: HUMAN OTC DRUG LABEL
Date: 20210203

ACTIVE INGREDIENTS: ALUMINUM CHLOROHYDRATE 3 g/100 mL
INACTIVE INGREDIENTS: ISOBUTANE; O-CYMEN-5-OL; .BETA.-CITRONELLOL, (R)-; GLYCYRRHIZA URALENSIS ROOT; BUTANE; ALCOHOL; PROPANE; PROPYLENE GLYCOL; HYDROXYCITRONELLAL; COUMARIN; PERILLA FRUTESCENS SEED; HELIANTHUS ANNUUS FLOWERING TOP

DEODORANT ANTIPERSPIRANT SPRAYS

DEODORANT ANTIPERSPIRANT SPRAYS

Active Ingredient(s)

ALUMINUM CHLOROHYDRATE 3g/100mL.

Purpose

Antiperspirant

Use

Reduces underarm wetness.

Warnings

For external use only.

Do not use

- on open skin wounds

When using this product keep out of eyes, ears, and mouth. In case of contact with eyes, rinse eyes thoroughly with water.
Stop use and ask a doctor if irritation or rash occurs. These may be signs of a serious condition.
Keep out of reach of children. If swallowed, get medical help or contact a Poison Control Center right away.

Stop use and ask a doctor if irritation or rash occurs. These may be signs of a serious condition.

Keep out of reach of children. If swallowed, get medical help or contact a Poison Control Center right away.

Directions

Gently shake several times before using. 15cm away from the skin, evenly sprayed in the armpit or other sweating parts.

Other information

- Store no more than 50℃

Inactive ingredients

o-CYMEN-5-OL
PROPANE
BUTANE
ALCOHOL
PROPYLENE GLYCOL
CITRONELLOL
COUMARIN
HYDROXYCITRONELLAL
ISOBUTANE
GLYCYRRHIZA URALENSIS (LICORICE) ROOT EXTRACT
PERILLA OCYMOIDES SEED EXTRACT
HELIANTHUS ANNUUS (SUNFLOWER) FLOWER EXTRACT